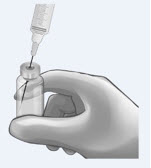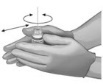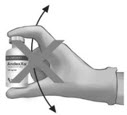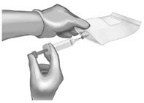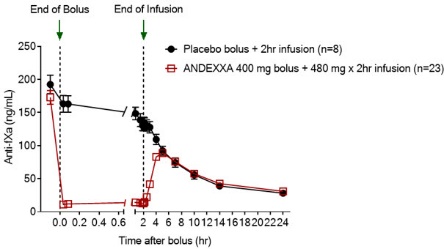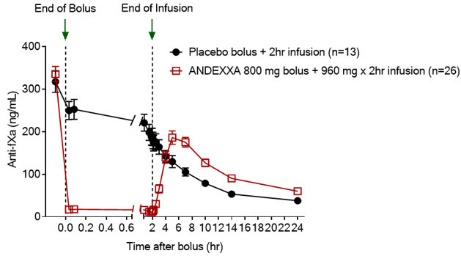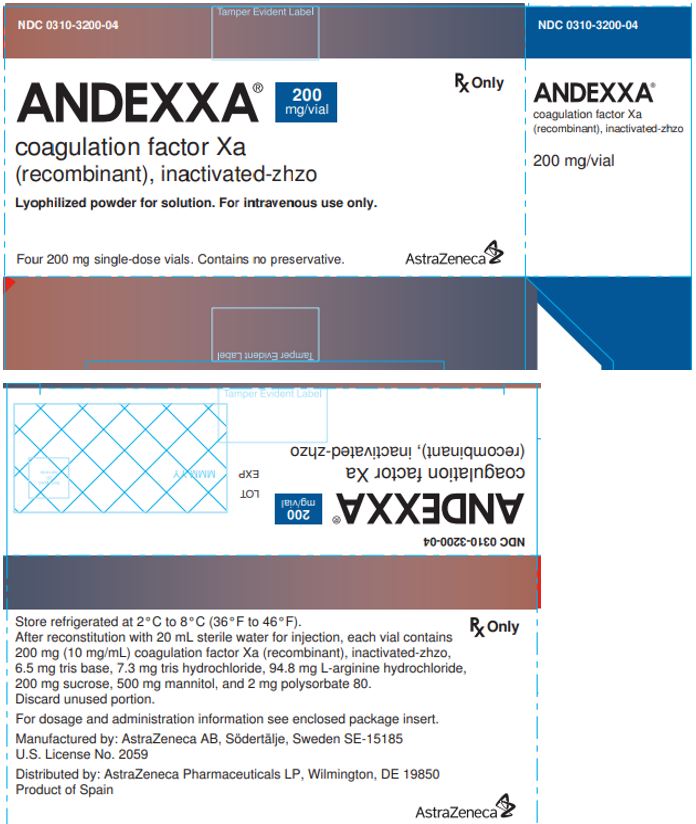 DRUG LABEL: ANDEXXA
NDC: 0310-3200 | Form: INJECTION, POWDER, LYOPHILIZED, FOR SOLUTION
Manufacturer: AstraZeneca Pharmaceuticals LP
Category: prescription | Type: HUMAN PRESCRIPTION DRUG LABEL
Date: 20250523

ACTIVE INGREDIENTS: andexanet alfa 200 mg/20 mL

HIGHLIGHTS OF PRESCRIBING INFORMATION

These highlights do not include all the information needed to use ANDEXXA safely and effectively. See Full Prescribing Information for ANDEXXA.
ANDEXXA® (coagulation factor Xa (recombinant), inactivated-zhzo)
Lyophilized powder for solution for intravenous injection
Initial U.S. Approval: 2018

RECENT MAJOR CHANGES

Warnings and Precautions (5.2) 03/2025

WARNING: THROMBOEMBOLIC RISKS, ISCHEMIC RISKS, CARDIAC ARREST, AND SUDDEN DEATHS

See full prescribing information for complete boxed warning

Treatment with ANDEXXA has been associated with serious and life-threatening adverse events, including: (5.1)

- Arterial and venous thromboembolic events
- Ischemic events, including myocardial infarction and ischemic stroke
- Cardiac arrest
- Sudden deaths

Monitor for thromboembolic events and initiate anticoagulation when medically appropriate. Monitor for symptoms and signs that precede cardiac arrest and provide treatment as needed.

1 INDICATIONS AND USAGE

ANDEXXA (coagulation factor Xa (recombinant), inactivated-zhzo) is a recombinant modified human factor Xa (FXa) protein indicated for patients treated with rivaroxaban or apixaban, when reversal of anticoagulation is needed due to life-threatening or uncontrolled bleeding. (1)

This indication is approved under accelerated approval based on the change from baseline in anti-FXa activity in healthy volunteers. An improvement in hemostasis has not been established. Continued approval for this indication may be contingent upon the results of studies that demonstrate an improvement in hemostasis in patients. (1, 14)

Limitations of Use

ANDEXXA has not been shown to be effective for, and is not indicated for, the treatment of bleeding related to any FXa inhibitors other than apixaban or rivaroxaban. (1)

2 DOSAGE AND ADMINISTRATION

For intravenous (IV) use only.

- Dose ANDEXXA based on the specific FXa inhibitor, dose of FXa inhibitor, and time since the patient's last dose of FXa inhibitor. (2)
- Administer as an IV bolus, with a target rate of 30 mg/min, followed by continuous infusion for 120 minutes. (2.3)
- There are two dosing regimens:

Dose [The safety and effectiveness of more than one dose have not been evaluated. (2.1)] | Initial IV Bolus | Follow-On IV Infusion
Low Dose | 400 mg at a target rate of 30 mg/min | 4 mg/min for 120 minutes
High Dose | 800 mg at a target rate of 30 mg/min | 8 mg/min for 120 minutes

3 DOSAGE FORMS AND STRENGTHS

ANDEXXA is available as a lyophilized powder in single-dose vials of 200 mg of coagulation factor Xa (recombinant), inactivated-zhzo. (3)

4 CONTRAINDICATIONS

None. (4)

5 WARNINGS AND PRECAUTIONS

- Arterial and venous thromboembolic events, ischemic events, and cardiac events, including sudden death, have occurred during treatment with ANDEXXA. Resume anticoagulant therapy as soon as medically appropriate following treatment with ANDEXXA. (5.1)
- Unresponsiveness to unfractionated heparin has been reported following ANDEXXA administration. (5.2)
- Re-elevation or incomplete reversal of anticoagulant activity can occur. (5.3)

6 ADVERSE REACTIONS

The most common adverse reactions (≥ 5%) in bleeding patients receiving ANDEXXA were urinary tract infections and pneumonia. (6.1)

To report SUSPECTED ADVERSE REACTIONS, contact AstraZeneca at 1-800-236-9933 or FDA at 1-800-FDA-1088 or www.fda.gov/medwatch.

7 DRUG INTERACTIONS

Do not use unfractionated heparin following ANDEXXA administration due to unresponsiveness characterized by non-prolongation of activated clotting times (7.1).

See full prescribing information for details on drug interactions.

FULL PRESCRIBING INFORMATION

WARNING: THROMBOEMBOLIC RISKS, ISCHEMIC RISKS, CARDIAC ARREST, AND SUDDEN DEATHS

Treatment with ANDEXXA has been associated with serious and life-threatening adverse events, including: (5.1)

- Arterial and venous thromboembolic events
- Ischemic events, including myocardial infarction and ischemic stroke
- Cardiac arrest
- Sudden deaths

Monitor for thromboembolic events and initiate anticoagulation when medically appropriate. Monitor for symptoms and signs that precede cardiac arrest and provide treatment as needed.

1 INDICATIONS AND USAGE

ANDEXXA is indicated for patients treated with rivaroxaban or apixaban, when reversal of anticoagulation is needed due to life-threatening or uncontrolled bleeding.

This indication is approved under accelerated approval based on the change from baseline in anti-FXa activity in healthy volunteers [see Clinical Studies (14)]. An improvement in hemostasis has not been established. Continued approval for this indication may be contingent upon the results of studies that demonstrate an improvement in hemostasis in patients.

Limitations of Use

ANDEXXA has not been shown to be effective for, and is not indicated for, the treatment of bleeding related to any FXa inhibitors other than apixaban or rivaroxaban.

2 DOSAGE AND ADMINISTRATION

2.1 Dose

For intravenous (IV) use only.

There are two dosing regimens (see Table 1). The safety and efficacy of an additional dose have not been established.

Table 1: ANDEXXA Dosing Regimens
Dose [The safety and effectiveness of more than one dose have not been evaluated.] | Initial IV Bolus | Follow-On IV Infusion | Total Number of 200 mg Vials
Low Dose | 400 mg at a target rate of 30 mg/min | 4 mg/min for 120 minutes (480 mg) | 5 (2 vials bolus + 3 vials infusion)
High Dose | 800 mg at a target rate of 30 mg/min | 8 mg/min for 120 minutes (960 mg) | 9 (4 vials bolus + 5 vials infusion)

The recommended dosing of ANDEXXA is based on the specific FXa inhibitor, dose of FXa inhibitor, and time since the patient's last dose of FXa inhibitor (see Table 2).

Table 2: ANDEXXA Dose Based on Rivaroxaban or Apixaban Dose (Timing of Last Dose of FXa Inhibitor before ANDEXXA Initiation)

FXa Inhibitor | FXa Inhibitor Last Dose | < 8 Hours or Unknown | ≥ 8 Hours
Rivaroxaban | ≤ 10 mg | Low Dose | Low Dose
Rivaroxaban | > 10 mg or Unknown | High Dose | Low Dose
Apixaban | ≤ 5 mg | Low Dose | Low Dose
Apixaban | > 5 mg or Unknown | High Dose | Low Dose

2.2 Reconstitution

- The reconstituted solution contains coagulation factor Xa (recombinant), inactivated-zhzo at a concentration of 10 mg/mL.
- Reconstituted ANDEXXA in vials is stable at room temperature for up to eight hours, or may be stored for up to 24 hours at 2°C to 8°C (36°F to 46°F).
- Reconstituted ANDEXXA in IV bags is stable at room temperature for up to eight hours.

IV Bolus Preparation

Determine total number of vials required (see Table 1).
200 mg vials:
Reconstitute the 200 mg vial of ANDEXXA with 20 mL of Sterile Water for Injection (SWFI).
Use a 20-mL (or larger) syringe and 20-gauge

(or smaller in diameter, e.g., 21-gauge) needle.
Slowly inject the SWFI, directing the solution onto the inside wall of the vial to minimize foaming.
To reduce the total reconstitution time needed during preparation, reconstitute all required vials in succession.

To ensure dissolution of the cake or powder, gently swirl each vial until complete dissolution of powder occurs (A). Do not shake (B); shaking could lead to foaming. Typical dissolution time for each vial is approximately three to five minutes. If dissolution is incomplete, discard the vial, and do not use the product.
Upon reconstitution, the parenteral drug product should be inspected visually for particulate matter and discoloration prior to administration.

(A)

(B)

Use 40-mL (or larger) syringe with a 20-gauge (or smaller in diameter, e.g., 21-gauge) needle to withdraw the reconstituted ANDEXXA solution from each of the vials until the required dosing volume

is achieved. Note the total volume withdrawn into the syringe.
Transfer the ANDEXXA solution from the syringe into an empty polyolefin or polyvinyl chloride IV bag with a volume of 250 mL or less.

Discard the syringe and needle.

Discard the vials, including any unused portion.

Continuous IV Infusion Preparation

- Follow the same procedure outlined above for IV bolus preparation. Reconstitute the total number of vials needed based on the dose requirements. More than one 40 to 60 mL syringe, or an equivalent 100-mL syringe, may be used for transfer of reconstituted solution to the IV bag.
- Infusion will require a 0.2 or 0.22 micron in-line polyethersulfone or equivalent low protein-binding filter.

2.3 Administration

- Upon reconstitution, the parenteral drug product should be inspected visually for particulate matter and discoloration prior to administration.
- Administer ANDEXXA intravenously, using a 0.2 or 0.22 micron in-line polyethersulfone or equivalent low protein-binding filter.
- Start the bolus at a target rate of approximately 30 mg/min.
- Within two minutes following the bolus dose, administer the continuous IV infusion for 120 minutes.

2.4 Restarting Anticoagulant Therapy

Patients treated with FXa inhibitor therapy have underlying disease states that predispose them to thromboembolic events. Reversing FXa inhibitor therapy exposes patients to the thrombotic risk of their underlying disease. To reduce the risk of thrombosis, resume anticoagulant therapy as soon as medically appropriate following treatment with ANDEXXA.

3 DOSAGE FORMS AND STRENGTHS

ANDEXXA is available as a white to off-white lyophilized powder in single-dose vials of 200 mg of coagulation factor Xa (recombinant), inactivated-zhzo.

4 CONTRAINDICATIONS

None.

5 WARNINGS AND PRECAUTIONS

5.1 Thromboembolic and Ischemic Risks

The thromboembolic and ischemic risks were assessed in 419 bleeding -patients in the ANNEXA-4 study who received ANDEXXA and were treated with apixaban or rivaroxaban. There were 45/419 (10.7%) patients who experienced a thrombotic event. The median time to first event was 10 days, and 17 patients experienced the event within three days of treatment. Of the 419 patients who received ANDEXXA, 266 received at least one anticoagulation dose within 30 days after treatment as a prophylactic measure. Of these 266 patients, 14 patients (5.3%) had a thrombotic event after resumption [see Adverse Reactions (6.1)].

Monitor patients treated with ANDEXXA for signs and symptoms of arterial and venous thromboembolic events, ischemic events, and cardiac arrest. To reduce thromboembolic risk, resume anticoagulant therapy as soon as medically appropriate following treatment with ANDEXXA [see Dosage and Administration (2.4)].

The safety of ANDEXXA has not been evaluated in patients who experienced thromboembolic events or disseminated intravascular coagulation within two weeks prior to the life-threatening bleeding event requiring treatment with ANDEXXA. Safety of ANDEXXA also has not been evaluated in patients who received prothrombin complex concentrates, recombinant factor VIIa, or whole blood products within seven days prior to the bleeding event.

5.2 Unresponsiveness to Unfractionated Heparin

Unresponsiveness to unfractionated heparin leading to non-prolongation of activated clotting times and serious thrombotic events has occurred following ANDEXXA administration. [see Postmarketing Experience (6.2)].

Do not use ANDEXXA for the reversal of direct FXa inhibitors (apixaban and rivaroxaban) prior to heparinization. If anticoagulation is needed, use an alternative anticoagulant to heparin

Use of ANDEXXA as an antidote for heparin has not been established.

5.3 Re-elevation or Incomplete Reversal of Anti-FXa Activity

The time course of anti-FXa activity following ANDEXXA administration was consistent among the healthy volunteer studies and the ANNEXA-4 study in bleeding patients [see Clinical Studies (14)]. Compared to baseline, there was a rapid and substantial decrease in anti-FXa activity corresponding to the ANDEXXA bolus. This decrease was sustained through the end of the ANDEXXA continuous infusion. The anti-FXa activity returned to the placebo levels approximately two hours after completion of a bolus or continuous infusion. Subsequently, the anti-FXa activity decreased at a rate similar to the clearance of the FXa inhibitors.

A total of 114 patients from ANNEXA-4 were anticoagulated with apixaban or rivaroxaban and had elevated baseline levels of anti-FXa (>150 ng/mL for apixaban and >300 ng/mL for rivaroxaban). After administration of ANDEXXA, these patients experienced decreased anti-FXa activity levels, with median reductions of 96% for rivaroxaban and 92% for apixaban.

6 ADVERSE REACTIONS

6.1 Clinical Trials Experience

Because clinical trials are conducted under widely varying conditions, adverse reaction rates observed in the clinical trials of a drug cannot be directly compared to rates in the clinical trials of another drug and may not reflect the rates observed in clinical practice.

The most common adverse reactions (≥ 5%) in bleeding patients receiving ANDEXXA were urinary tract infections and pneumonia.

In Study 3 (ANNEXA-4), four hundred and seventy-seven patients with acute major bleeding were enrolled and received ANDEXXA. Of these 477 patients, 419 patients were treated with apixaban (245/419; 58.5%) or rivaroxaban (174/419; 41.5%). Most patients had received apixaban or rivaroxaban as anticoagulation treatment for atrial fibrillation (348/419; 83%) or venous thromboembolism (65/419; 16%). In the majority of patients, ANDEXXA was used to reverse anticoagulant therapy following either an intracranial hemorrhage (289/419; 69%) or a gastrointestinal bleed (95/419; 23%), with the remaining patients (35/419; 8.4%) experiencing bleeding at other sites. Patients were assessed at a Day 30 follow-up visit following infusion with ANDEXXA.

Deaths

In the ANNEXA-4 study, of the 419 patients in the safety population who were treated with apixaban or rivaroxaban, there were 75 deaths (18%). There were 37 cardiovascular deaths related to bleeding, 19 deaths that were cardiovascular and not related to bleeding, 14 that were non-cardiovascular, and 5 deaths had an uncertain or unknown cause. The average time to death was 15 days after treatment. All patients died prior to Day 45. Of the 75 patients who died, the initial bleeding event was intracranial bleeding in 55 (73%), gastrointestinal bleeding in 14 (19%), and other bleeding types in 6 (8%)patients.

Thromboembolic and Ischemic Events

In the Study 3 (ANNEXA-4), 45/419 (10.7%) patients experienced one or more of the following thromboembolic events: cerebrovascular accident (CVA) (19/45; 42%), deep venous thrombosis (11/45; 24%), myocardial infarction (9/45; 20%), pulmonary embolism (5/45; 11%), and transient ischemic attack (1/45; 2%). The median time to event was ten days. A total of 38% of patients with thromboembolic events (17/45) experienced the thromboembolic event during the first three days. Of the 419 patients who received ANDEXXA, 282 (67.3%) received any form of re-anticoagulation within 30 days after treatment. Of these 282 patients, 16 received anticoagulation in response to a thrombotic event, while 266 received the anticoagulation as a prophylactic. Of these 266, 14 patients (5.3%) had a thrombotic event after resumption of anticoagulation; while of the 153 patients who did not receive anticoagulation as a prophylactic, 31 (20.3%) had a thrombotic event. No patient had a thrombotic event after resumption of oral anticoagulation [see Warnings and Precautions (5.1)].

Infusion-Related Reactions

In the ANNEXA-4 study, 2/419 (0.5%) patients experienced an infusion-related reaction, neither of which were assessed as severe (1 moderate; 1 mild). Reported signs and symptoms were transient and included rigors, chills, hypertension, oxygen desaturation, agitation and confusion.

6.2 Postmarketing Experience

The following adverse reactions have been identified during post-approval use of ANDEXXA.

Because these reactions are reported voluntarily from a population of uncertain size, it is not always possible to reliably estimate their frequency or stablish a causal relationship to drug exposure.

General disorders and administration site conditions: heparin resistance [see Unresponsiveness to Unfractionated Heparin (5.2)] and [see Use with Unfractionated Heparin (7.1)].

7 DRUG INTERACTIONS

7.1 Use with Unfractionated Heparin

Unresponsiveness to unfractionated heparin has occurred following ANDEXXA administration, characterized by non-prolongation of activated clotting times and requirement for increased dosing of heparin. Do not use unfractionated heparin following ANDEXXA administration.

7.2 Interference with Anti-FXa Activity Test

Current commercial clinical anti-FXa-activity assays are unsuitable for measuring FXa activity following administration of ANDEXXA. Due to the reversible binding of ANDEXXA to the FXa inhibitor, the high sample dilution currently used in commercial clinical assays promotes dissociation of the inhibitor from ANDEXXA, resulting in detection of erroneously elevated anti-FXa activity levels, thereby causing a underestimation of the reversal activity of ANDEXXA.

8 USE IN SPECIFIC POPULATIONS

8.1 Pregnancy

Risk Summary

There are no adequate and well-controlled studies of ANDEXXA in pregnant women to inform patients of associated risks. Animal reproductive and developmental studies have not been conducted with ANDEXXA.

In the U.S. general population, the estimated background risk of major birth defects and miscarriage in clinically recognized pregnancies is 2% to 4% and 15% to 20%, respectively.

Labor or Delivery

The safety and effectiveness of ANDEXXA during labor and delivery have not been evaluated.

8.2 Lactation

Risk Summary

There is no information regarding the presence of ANDEXXA in human milk, the effects on the breastfed child, or the effects on milk production.

The developmental and health benefits of breastfeeding should be considered along with the mother's clinical need for ANDEXXA and any potential adverse effects on the breastfed child from ANDEXXA or from the underlying maternal condition.

8.4 Pediatric Use

The safety and efficacy of ANDEXXA in the pediatric population have not been studied.

8.5 Geriatric Use

Of the 419 patients in the ANNEXA-4 study of ANDEXXA, 381 (91%) were 65 years of age or older, and 278 (66%) were older than 75 years of age. No overall differences in safety or efficacy were observed between these patients and younger patients, and other reported clinical experience has not identified differences in responses between elderly and younger patients; however, greater sensitivity of some older individuals cannot be ruled out.

11 DESCRIPTION

ANDEXXA (coagulation factor Xa (recombinant), inactivated-zhzo) is a sterile, white to off-white lyophilized powder available in single-dose vials.

Each 200 mg vial delivers 200 mg of coagulation factor Xa formulated with the inactive ingredients tromethamine (Tris base), Tris hydrochloride, L-arginine hydrochloride, sucrose (1% w/v), mannitol (2.5% w/v), and polysorbate 80 (0.01% w/v) at pH 7.8.

After reconstitution of the lyophilized powder with SWFI for IV administration, the product is a clear, colorless to slightly yellow solution. ANDEXXA contains no preservatives.

The active ingredient in ANDEXXA is a genetically modified variant of human FXa. The active site serine was substituted with alanine, rendering the molecule unable to cleave and activate prothrombin. The gamma-carboxyglutamic acid (Gla) domain was removed to eliminate the protein's ability to assemble into the prothrombinase complex, thus removing the potential anticoagulant effects.

No additives of human or animal origin are used in the manufacture of ANDEXXA. The recombinant protein is produced in a genetically engineered Chinese Hamster Ovary (CHO) cell expression system and has a molecular weight of approximately 41 kDa. The manufacturing process incorporates two validated virus clearance steps.

12 CLINICAL PHARMACOLOGY

12.1 Mechanism of Action

Coagulation factor Xa (recombinant), inactivated-zhzo exerts its procoagulant effect by binding and sequestering the FXa inhibitors, rivaroxaban and apixaban. Another observed procoagulant effect of the ANDEXXA protein is its ability to bind to, and inhibit the activity of, Tissue Factor Pathway Inhibitor (TFPI). Inhibition of TFPI activity can increase tissue factor (TF)-initiated thrombin generation.

12.2 Pharmacodynamics

The effects of ANDEXXA can be measured using assays for its anti-FXa activity, free fraction of FXa inhibitor, and thrombin generation. In addition to its ability to sequester the FXa inhibitors, rivaroxaban and apixaban, ANDEXXA has been shown to inhibit TFPI activity.

The dose and dosing regimen of ANDEXXA that are required to reverse anti-FXa activity and to restore thrombin generation were determined in dose-ranging studies on healthy volunteers. Dosing of ANDEXXA, as a bolus followed by a two-hour continuous infusion, resulted in a rapid decrease in anti-FXa activity (within two minutes after the completion of the bolus administration) followed by reduced anti-FXa activity that was maintained throughout the duration of the continuous infusion [see Clinical Studies (14)]. The anti-FXa activity returned to the placebo levels approximately two hours after completion of a bolus or continuous infusion, whereas TFPI activity in plasma returned to the pretreatment levels approximately 96 hours following ANDEXXA administration.

Elevation of TF-initiated thrombin generation above the baseline range (prior to anticoagulation) occurred within two minutes following a bolus administration of ANDEXXA and was maintained throughout the duration of the continuous infusion. The TF-initiated thrombin generation was elevated above placebo for at least 22 hours. The sustained elevation of thrombin generation over the baseline range and the sustained elevation over placebo were not observed in a contact-activated thrombin generation assay (an assay that is not affected by TF-TFPI interaction).

Laboratory assessment of coagulation does not necessarily correlate with or predict the hemostatic effectiveness of ANDEXXA.

12.3 Pharmacokinetics

A summary of the pharmacokinetic (PK) properties of ANDEXXA in healthy patients is shown in the table below (see Table 3).

Table 3: Summary of PK Parameters with High and Low Doses
 | Low Dose | High Dose
n | 11 | 10
AUC0-∞; (hr*µg/mL) | 200.5 (16.3) [153.4; 255.6] | 572.9 (16.0) [467.1; 783.9]
Cmax; (µg/mL) | 76.6 (17.5) [61.1; 100.1] | 206.6 (18.8) [158.9; 280.5]
Clearance; (L/hr) | 4.4 (16.3) [3.4; 5.7] | 3.1 (16.0) [2.3; 3.8]
T1/2 (hr) | 3.3 (15.0) [2.3; 4.0] | 2.7 (20.0) [1.9; 3.4]
Vss (L) | 4.4 (17.6) [3.3; 5.7] | 3.0 (23.3) [2.2; 5.0]
Data presented are geometric mean (Geometric Mean % Coefficient of Variation), [range].

Drug-Drug Interaction

The pharmacokinetics of ANDEXXA were not affected by apixaban (5 mg orally BID for six days) or rivaroxaban (20 mg orally once daily for six days).

12.6 Immunogenicity

The observed incidence of anti-drug antibodies (ADAs) is highly dependent on the sensitivity and specificity of the assay. Differences in assay methods preclude meaningful comparisons of the incidence of ADAs in the studies described below with the incidence of ADAs in other studies, including those of ANDEXXA.

Using electrochemiluminescence (ECL)-based assays, 417 ANDEXXA-treated healthy patients were tested for antibodies to ANDEXXA as well as for antibodies cross-reacting with factor X (FX) and FXa. The analysis of available samples up to Day 48 from pooled healthy patients revealed low incidence of anti-ANDEXXA (≤ 8.7%) and anti-FXa (≤ 0.8%) at all timepoints and no anti-FX antibody was detected at any timepoint. The pattern of immunogenicity in patients with acute major bleeding in the ANNEXA-4 study was similar to that observed in healthy patients. Of the 277 ANDEXXA-treated patients in ANNEXA-4 who had available samples at Day 30 or 45, 7.9% (22/277) had antibodies against ANDEXXA, 0.4% (1/277) patients had antibodies against FXa and no patients had antibodies against FX. No neutralizing antibodies against ANDEXXA or cross-reacting with FX or FXa were detected in healthy patients or in bleeding patients.

Because of the low occurrence of anti-drug antibodies, the effect of these antibodies on the pharmacokinetics, pharmacodynamics, safety, and/or effectiveness of ANDEXXA have not been fully characterized.

13 NONCLINICAL TOXICOLOGY

13.1 Carcinogenesis, Mutagenesis, Impairment of Fertility

No animal studies were performed to evaluate the effects of ANDEXXA on carcinogenesis, mutagenesis, or impairment of fertility.

14 CLINICAL STUDIES

The safety and efficacy of ANDEXXA were evaluated in two prospective, randomized, placebo- controlled studies, conducted in healthy volunteers (Study 1 ANNEXA-A; Study 2 ANNEXA-R). Both studies examined the percent change in anti-FXa activity, from baseline to nadir, for the low-dose and high-dose regimens of bolus followed by continuous infusion. Nadir is defined as the smallest value measured within five minutes after the end of the continuous infusion.

The safety and efficacy of ANDEXXA were evaluated in a multinational, prospective, single-arm, open-label study (Study 3 ANNEXA-4) in patients presenting with acute major bleeding and who have recently received an FXa inhibitor. This study examined the percent change in anti-FXa activity from baseline to the nadir between five minutes after the end of the bolus up until the end of the infusion and the rate of effective hemostasis within 12 hours after infusion, as rated by an independent endpoint adjudication committee.

Study 1 ANNEXA-A (NCT02207725) – apixaban reversal

In Study 1, healthy patients (median age: 57 years; range: 50 to 73 years) received apixaban 5 mg twice daily for three and a half days to achieve steady-state. At three hours after the last apixaban dose (~ Cmax), ANDEXXA or placebo was administered. Eight patients received placebo, and 24 received ANDEXXA, administered as a 400 mg IV bolus followed by a 4 mg per minute continuous infusion for 120 minutes (total 480 mg).

Study 2 ANNEXA-R (NCT02220725) – rivaroxaban reversal

In Study 2, healthy patients (median age: 57 years; range: 50 to 68 years) received rivaroxaban 20 mg once per day for four days to achieve steady-state. At four hours after the last rivaroxaban dose (~ Cmax), ANDEXXA or placebo was administered. Thirteen patients received placebo, and 26 received ANDEXXA, administered as an 800 mg IV bolus followed by an 8 mg per minute continuous infusion for 120 minutes (total 960 mg).

Reduction in Anti-FXa Activity

In Study 1 and Study 2, the percent change from baseline in anti-FXa activity at its nadir was statistically significant (p < 0.0001) in favor of the ANDEXXA groups compared to placebo in both Studies 1 and 2. The results of Study 1 and Study 2 are provided below (see Table 4).

The time courses of anti-FXa activity before and after ANDEXXA administration are shown in Figure 1.

Table 4 - A: Change in Anti-FXa Activity/Study 1 (apixaban)
Anti-FXa Activity | ANDEXXA n=23 | Placebo n=8
Mean baseline ng/mL (± SD) | 173.0 (50.5) | 191.7 (34.4)
Mean ng/mL (± SD) change from baseline at the nadir [Nadir is the smallest value for anti-FXa activity at the 110-minute (ten minutes prior to the end of the infusion) time point, 2-minute time point before completion of the infusion, or the 5-minute time point after the completion of the infusion for each patient.] | -160.6 (49.3) | -63.2 (18.1)
Mean % (± SD) change from baseline at the nadir | -92.3 (2.8) | -32.7 (5.6)
Median difference and associated; 95% confidence interval (CI) [The CI is for the Hodges-Lehman estimate of shift.] | -59.5 (-64.1; -55.2) | not applicable
p-value | < 0.0001 [p-value obtained from a 2-sided exact Wilcoxon rank-sum test.] | not applicable

Table 4 - B: Change in Anti-FXa Activity/Study 2 (rivaroxaban)
Anti-FXa Activity | ANDEXXA n=26 | Placebo n=13
Mean baseline ng/mL (± SD) | 335.3 (91.0) | 317.2 (91.0)
Mean ng/mL (± SD) change from baseline at the nadir [Nadir is the smallest value for anti-FXa activity at the 110-minute (ten minutes prior to the end of the infusion) time point, 2-minute time point before completion of the infusion, or the 5-minute time point after the completion of the infusion for each patient.] | -324.5 (89.2) | -143.4 (58.8)
Mean % (± SD) change from baseline at the nadir | -96.7 (1.8) | -44.6 (11.8)
Median difference and associated; 95% confidence interval (CI) [The CI is for the Hodges-Lehman estimate of shift.] | -51.9 (-58.0; -47.0) | not applicable
p-value | < 0.0001 [p-value obtained from a 2-sided exact Wilcoxon rank-sum test.] | not applicable
SD = Standard deviation.
Note: Baseline is the last assessment obtained prior to the first dose of ANDEXXA or placebo.

Figure 1: Change in Anti-FXa Activity (ng/mL) in Patients Anticoagulated with Apixaban (A – Study 1) and Rivaroxaban (B – Study 2)

(A)

(B)

Anti-FXa activity was measured prior to and after ANDEXXA or placebo administration.
Dashed lines indicate the end of the bolus or infusion. A break in the x-axis is added to better visualize the immediate, short-term dynamics of anti-FXa activity following ANDEXXA treatment. The points on the graph represent the mean anti-FXa activity level; error bars illustrate standard error. There was a statistically significant difference (p < 0.05) in the percent change of anti-FXa activity normalized to pre-bolus between ANDEXXA and placebo until two hours after administration of infusion.
A. Apixaban – with ANDEXXA 400 mg IV bolus plus 4 mg/min infusion for 120 minutes.
B. Rivaroxaban – with ANDEXXA 800 mg IV bolus plus 8 mg/min infusion for 120 minutes.

Study 3 ANNEXA-4 (NCT02329327)

In a multinational, prospective, single-arm, open-label study, ANDEXXA was administered to 477

patients taking FXa inhibitors who presented with acute major bleeding.

The co-primary endpoints are: (a) percent change in anti-FXa activity from baseline to the nadir

between five minutes after the end of the bolus up until the end of the infusion; and (b) rate of

effective hemostasis within 12 hours after infusion, as rated by an independent endpoint

adjudication committee.

For the 477 patients dosed with ANDEXXA, 302 were efficacy-evaluable defined as patients (1)

on treatment with apixaban or rivaroxaban; (2) who had a baseline anti-FXa activity above 75

ng/mL; and (3) were adjudicated as meeting eligibility criteria for acute major bleeding [see

Adverse Reactions (6)].

For anti-FXa activity, the median (95% CI) decrease from baseline to nadir in anti-FXa activity for

apixaban was -93% (-94%; -92%) and for rivaroxaban was -94% (-95%; -93%).

An improvement in hemostasis has not been established. ANDEXXA has not been shown to be

effective for bleeding related to any FXa inhibitors other than apixaban or rivaroxaban.

16 HOW SUPPLIED/STORAGE AND HANDLING

How Supplied

ANDEXXA (coagulation factor Xa (recombinant), inactivated-zhzo) is a white to off-white lyophilized cake or powder supplied as single-dose vials in a carton. ANDEXXA is not made with natural rubber latex.

ANDEXXA vials are provided as follows (see Table 5):

Table 5: Presentation of ANDEXXA
NDC | Carton Configuration | Vial Cap Color | Packaging Color
NDC 0310-3200-04 | 4 single use vials in a carton, each vial containing 200 mg of ANDEXXA | Vials have a red flip-off cap. | 1. Carton and vial label have a red to blue transition colored stripe across the front. 2. Carton and label have "200 mg/vial" in a blue graphic on the front panel.
NDC 0310-3200-05 | 5 single use vials in a carton, each vial containing 200 mg of ANDEXXA | Vials have a red flip-off cap. | 1. Carton and vial label have a red to blue transition colored stripe across the front. 2. Carton and label have "200 mg/vial" in a blue graphic on the front panel.

Storage and Handling

Prior to reconstitution

Unopened vials should be stored refrigerated at 2°C to 8°C (36°F to 46°F) until the expiration date indicated on the label. DO NOT FREEZE. Do not use ANDEXXA after the expiration date.

After reconstitution

- Reconstituted ANDEXXA in vials is stable at room temperature for up to 8 hours, or may be stored for up to 24 hours at 2°C to 8°C (36°F to 46°F).
- Reconstituted ANDEXXA in IV bags is stable at room temperature for up to 8 hours.
- Discard any unused portion of reconstituted solution.

17 PATIENT COUNSELING INFORMATION

Discuss following with the patient and /or caregivers:

- Thromboembolic and Ischaemic Risks: Inform patients and/or caregivers that the reversing of FXa inhibitor therapy increases the risk of thromboembolic events. Arterial and venous thromboembolic events, ischemic events, cardiac events, and sudden death were observed within 30 days following ANDEXXA administration.[see Warnings and Precautions (5.1)].
- Unresponsiveness to Unfractionated Heparin: Inform patients and/or caregivers that unresponsiveness to unfractionated heparin and serious thrombotic events have occurred following ANDEXXA administration. [see Warnings and Precautions (5.2)].

Manufactured by:

AstraZeneca AB

Södertälje, Sweden SE-15185

Distributed by:

AstraZeneca Pharmaceuticals LP

Wilmington, DE 19850

U.S. License No. 2059

Product of Spain

ANDEXXA is a registered trademark of the AstraZeneca group of companies.

©AstraZeneca 2024

PRINCIPAL DISPLAY PANEL - 200 mg Vial Carton

NDC 0310-3200-04 Rx Only

ANDEXXA® 200mg/vial
coagulation factor Xa
(recombinant), inactivated-zhzo

Lyophilized powder for solution. For intravenous use only.

Four 200 mg single-dose vials. Contains no preservative. AstraZeneca